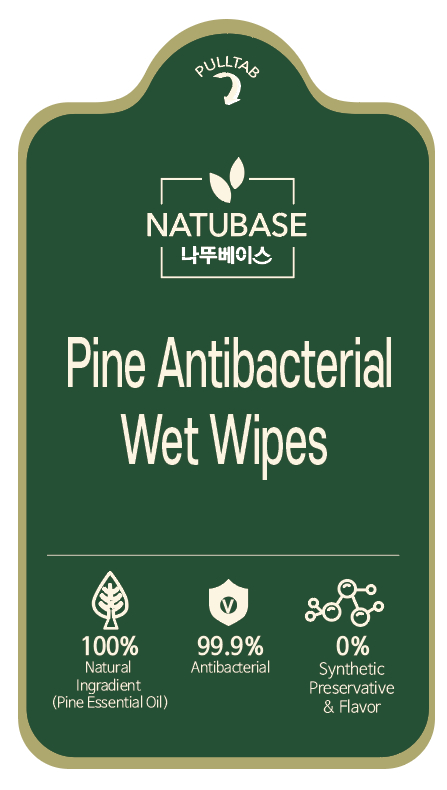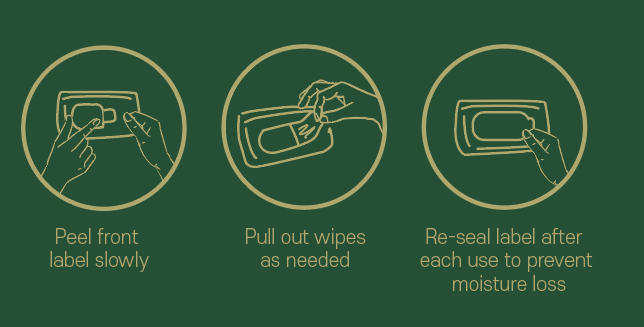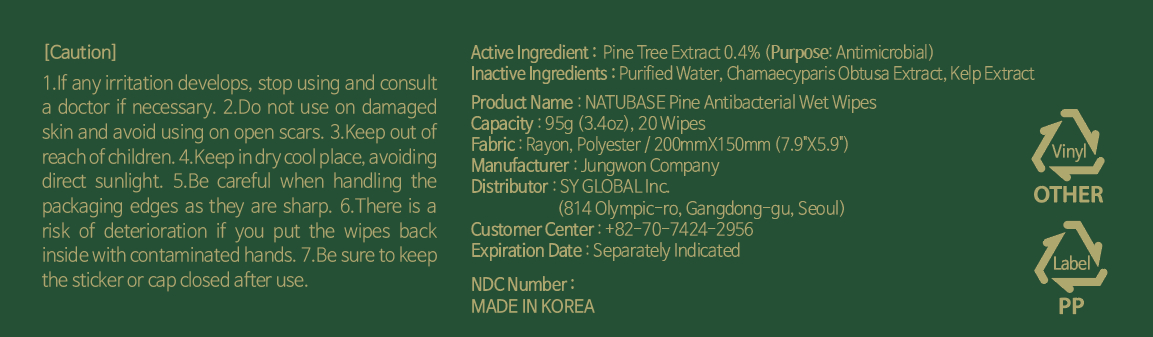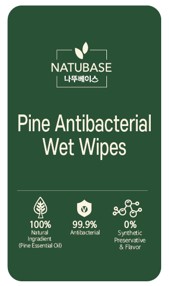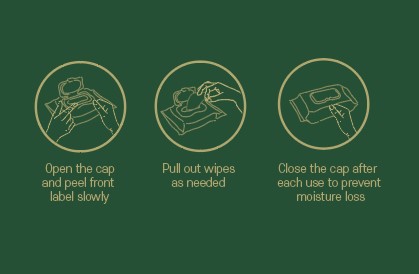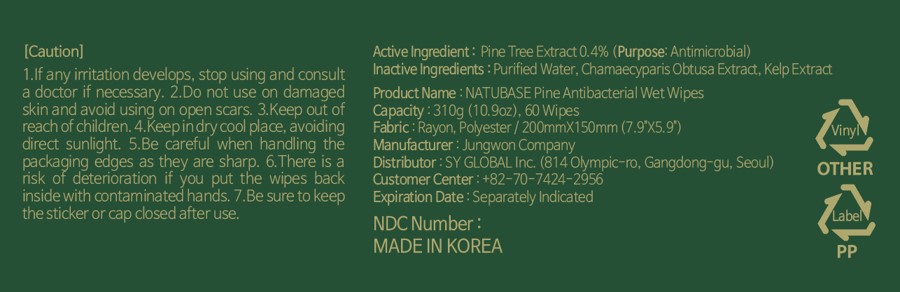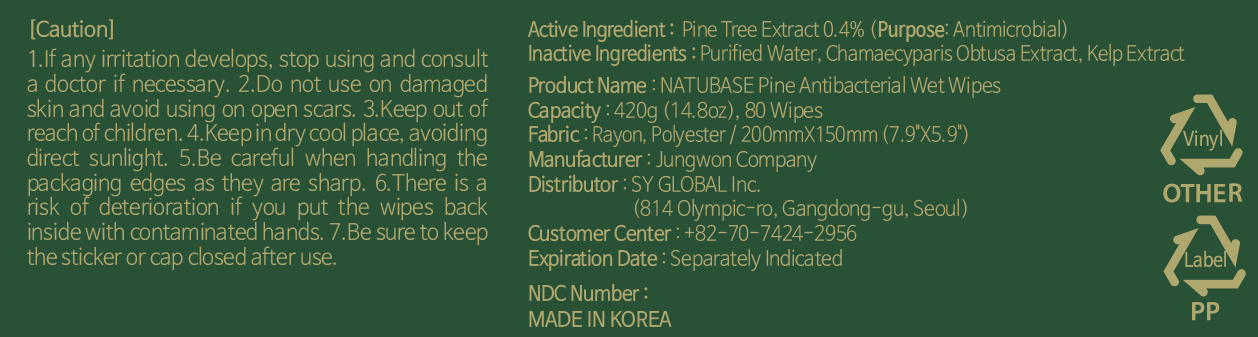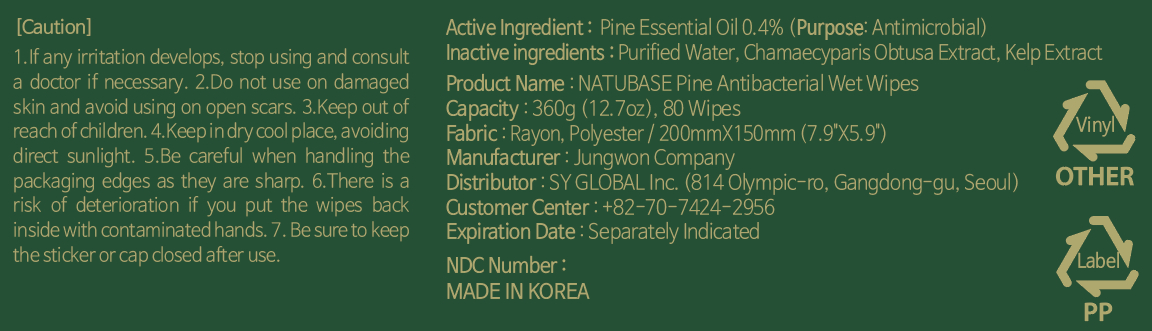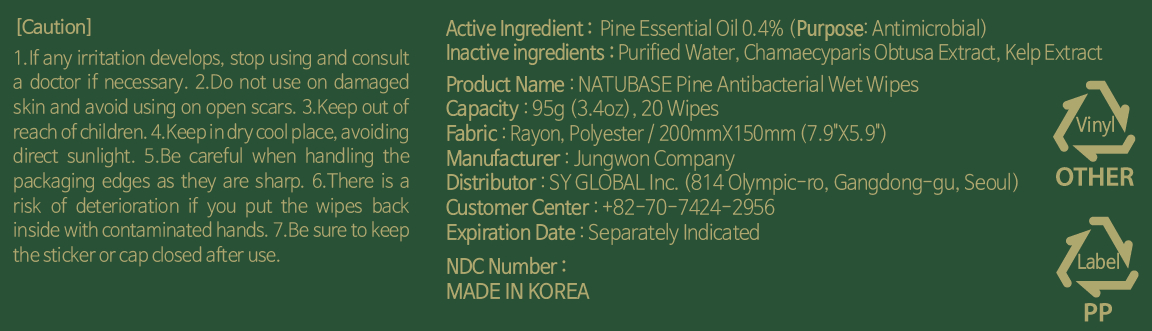 DRUG LABEL: NATUBASE Pine Antibacterial Wet Wipes
NDC: 77200-001 | Form: LIQUID
Manufacturer: SY Global Inc
Category: otc | Type: HUMAN OTC DRUG LABEL
Date: 20200609

ACTIVE INGREDIENTS: PINUS DENSIFLORA WHOLE 0.4 g/100 g
INACTIVE INGREDIENTS: CHAMAECYPARIS OBTUSA WHOLE; WATER; LAMINARIA JAPONICA

Active Ingredient

Pine Tree Extract 0.4%

Purpose

Antimicrobial

Inactive Ingredients

WATER(Purified Water), LAMINARIA JAPONICA(Kelp Extract), CHAMAECYPARIS OBTUSA WHOLE(Chamaecyparis Obtusa Extract)

Use

Peel front label slowly
Pull out wipes as needed

Use

Re-seal label after each use to prevent moisture loss

Caution

If any irritation develops, stop using and consult a doctor if necessary.

Caution

Do not use on damaged skin and avoid using on open scars.

Caution

Keep out of reach of children.

Caution

Keep in dry cool place, avoiding direct sunlight.

Be careful when handling the packaging edges as they are sharp.

Caution

There is a risk of deterioration if you put the wipes back inside with contaminated hands.

Caution

Be sure to keep the sticker or cap closed after use.